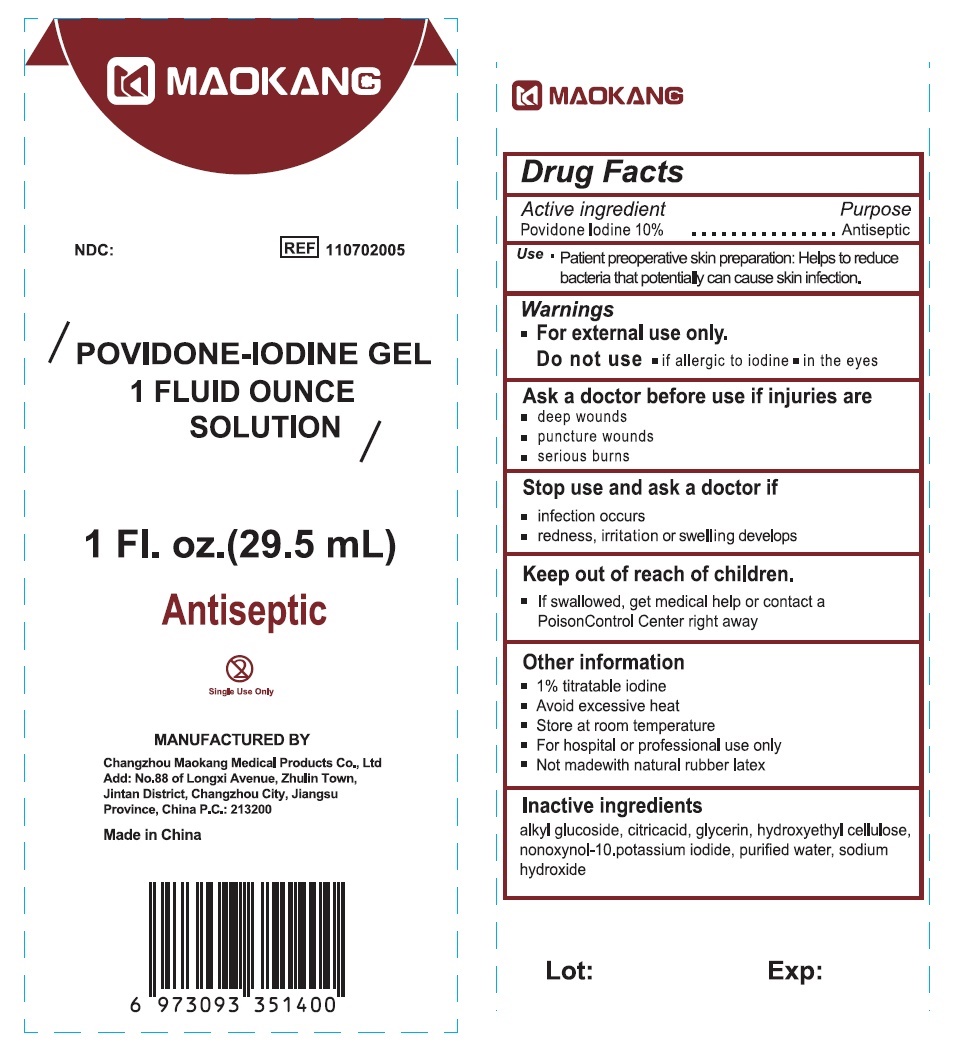 DRUG LABEL: Maokang Povidone Iodine
NDC: 59050-802 | Form: LIQUID
Manufacturer: Changzhou Maokang Medical Products Co., Ltd
Category: otc | Type: HUMAN OTC DRUG LABEL
Date: 20240626

ACTIVE INGREDIENTS: POVIDONE-IODINE 100 mg/1 mL
INACTIVE INGREDIENTS: CITRIC ACID MONOHYDRATE; GLYCERIN; HYDROXYETHYL CELLULOSE, UNSPECIFIED; NONOXYNOL-10; POTASSIUM IODIDE; WATER; SODIUM HYDROXIDE

Maokang Povidone-Iodine Gel

Active ingredient

Povidone Iodine 10%

Purpose

Antiseptic

Use

- Patient preoperative skin preparation: Helps to reduce bacteria that potentially can cause skin infection.

DOSAGE AND ADMINISTRATION

Patient preoparative skin preparation

Warnings

- For external use only.

Do not use

- if allergic to iodine
- in the eyes

Ask a doctor before use if injuries are

- deep wounds
- puncture wounds
- serious burns

Stop use and ask a doctor if

- infection occurs
- redness, irritation or swelling develops

Keep out of reach of children.

- If swallowed, get medical help or contact a Poison Control Center right away

Other information

- 1% titratable iodine
- Avoid excessive heat
- Store at room temperature
- For hospital or professional use only
- Not madewith natural rubber latex

Inactive ingredients

alkyl glucoside, citricacid, glycerin, hydroxyethyl cellulose, nonoxynol-10, potassium iodide, purified water, sodium hydroxide